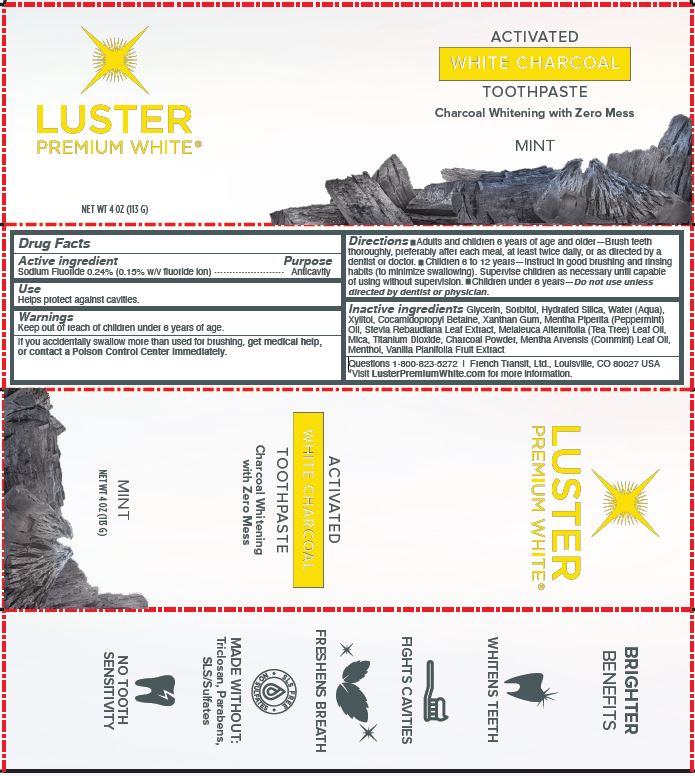 DRUG LABEL: LUSTER PREMIUM WHITE
NDC: 72805-201 | Form: GEL, DENTIFRICE
Manufacturer: French Transit, Ltd.
Category: otc | Type: HUMAN OTC DRUG LABEL
Date: 20201024

ACTIVE INGREDIENTS: SODIUM FLUORIDE .24 g/100 g
INACTIVE INGREDIENTS: GLYCERIN; SORBITOL; HYDRATED SILICA; WATER; XYLITOL; COCAMIDOPROPYL BETAINE; XANTHAN GUM; PEPPERMINT OIL; STEVIA REBAUDIUNA LEAF; TEA TREE OIL; MICA; TITANIUM DIOXIDE; ACTIVATED CHARCOAL; MENTHA ARVENSIS LEAF OIL; MENTHOL; VANILLA BEAN

LUSTER PREMIUM WHITE

ACTIVE INGREDIENT

SODIUM FLUORIDE 0.24% (0.15% W/V FLUORIDE ION)

PURPOSE

ANTI-CAVITY

USE

HELPS PROTECT AGAINST CAVITIES.

WARNINGS

If you accidentally swallow more than used for brushing, get medical help,

Keep out of reach of children under 6 years of age.

DIRECTIONS

- Adults and children 6 years of age and older—Brush teeth thoroughly, preferably after each meal, at least twice daily, or as directed by adentist or doctor.
- Children 6 to 12 years—Instruct in good brushing and rinsing habits (to minimize swallowing). Supervise children as necessary until capable of using without supervision.
- Children under 6 years—Do not use unless directed by dentist or physician.

INACTIVE INGREDIENTS

Glycerin, Sorbitol, Hydrated Silica, Water (Aqua), Xylitol, Cocamidopropyl Betaine, Xanthan Gum, Mentha Piperita (Peppermint) Oil, Stevia Rebaudiana Leaf Extract, Melaleuca Alternifolia (Tea Tree) Leaf Oil, Mica, Titanium Dioxide, Charcoal Powder, Mentha Arvensis (Cornmint) Leaf Oil, Menthol, Vanilla Planifolia Fruit Extract

QUESTIONS

1-800-823-5272 | French Transit, Ltd., Louisville, CO 80027 USA
*Visit LusterPremiumWhite.com for more information.